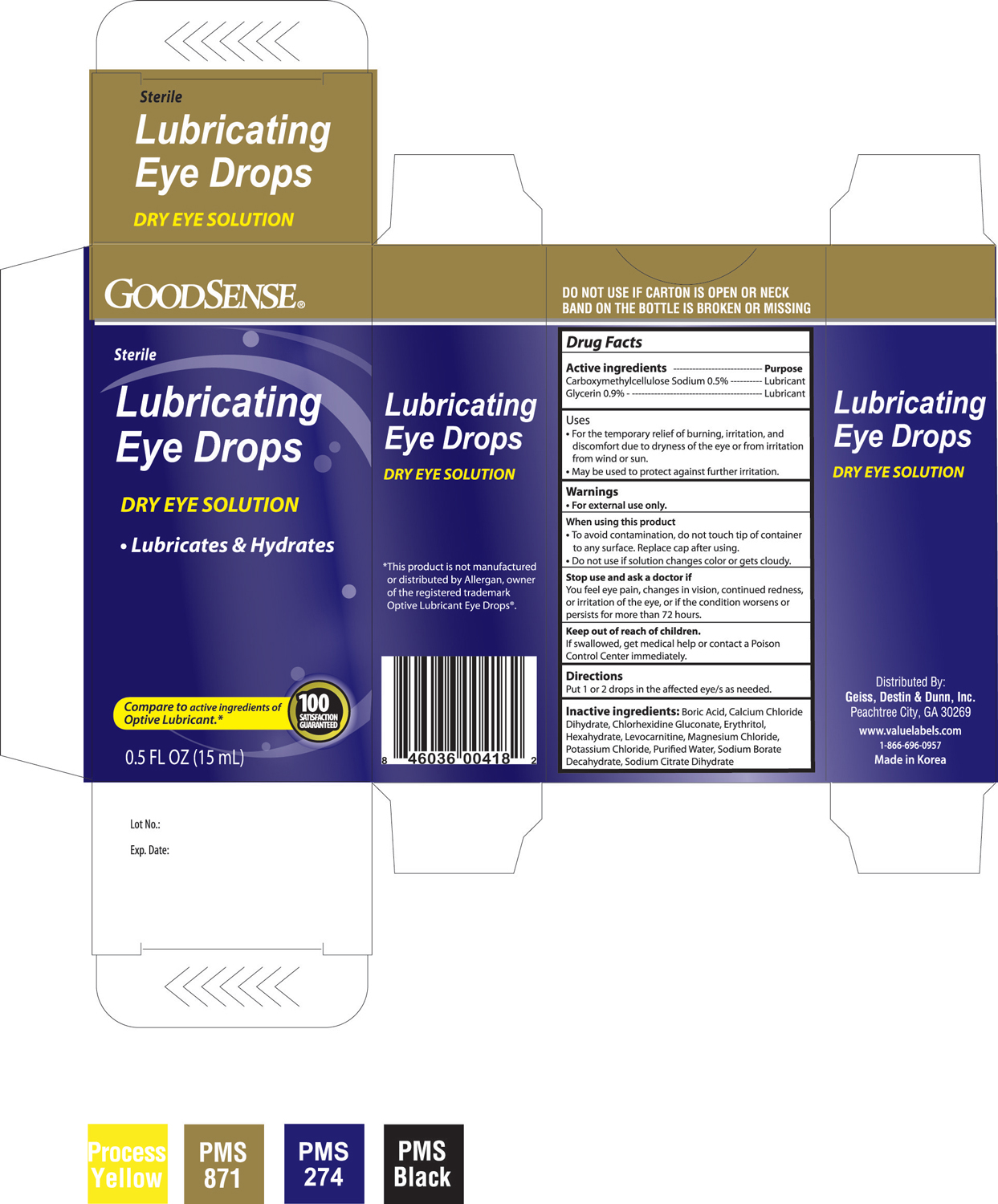 DRUG LABEL: GOODSENSE LUBRICATING EYE DROPS
NDC: 11716-0041 | Form: SOLUTION
Manufacturer: HANLIM PHARM. CO., LTD.
Category: otc | Type: HUMAN OTC DRUG LABEL
Date: 20100730

ACTIVE INGREDIENTS: CARBOXYMETHYLCELLULOSE SODIUM 5 mg/1 mL; GLYCERIN 9 mg/1 mL
INACTIVE INGREDIENTS: BORIC ACID; CALCIUM CHLORIDE ; CHLORHEXIDINE GLUCONATE; ERYTHRITOL; LEVOCARNITINE; MAGNESIUM CHLORIDE; POTASSIUM CHLORIDE; WATER; SODIUM BORATE 

DRUG FACTS

ACTIVE INGREDIENT

Active ingredients----------------------------------------------------------Purpose

Carboxymethylcellulose Sodium 0.5%----------------------------Lubricant

Glycerin 0.9%---------------------------------------------------------------Lubricant

Uses

- For the temporary relief of burning, irritation, and discomfort due to dryness of the eye or from irritation from wind or sun.
- May be sued to protect against further irritation.

Warnings

- For external use only.

When using this product

- To avoid contamination, do not touch tip of container to any surface. Replace cap after using.
- Do not use if solution changes color or gets cloudy.

Stop use and ask a doctor if

You feel eye pain, changes in vision, continued redness, or irritation of the eye, or if the condition worsens or persists for more than 72 hours.

Keep out of reach of children.

If swallowed, get medical help or contact a Poison Control Center immediately.

Directions

Put 1 or 2 drops in the affected eye/s as needed.

INACTIVE INGREDIENT

Inactive ingredients: Boric Acid, Calcium Chloride Dihydrate, Chlorhexidine Gluconate, Erythritol Hexahydrate, Levocarnitine, Magnesium Chloride, Potassium Chloride, Purified Water, Sodium Borate Decahydrate, Sodium Citrate Dihydrate

PACKAGE LABEL

Enter section text here